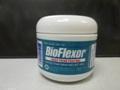 DRUG LABEL: BioFlexor
NDC: 62391-001 | Form: GEL
Manufacturer: Health Care Laboratories Inc.
Category: otc | Type: HUMAN OTC DRUG LABEL
Date: 20140521

ACTIVE INGREDIENTS: MENTHOL 0.03 g/1 g
INACTIVE INGREDIENTS: WATER

DOSAGE AND ADMINISTRATION

Apply BioFlexor gel onto the affected area(s) up to 3 to 4 times daily as needed. Apply sufficient amount at bedtime for a restful sleep and in the morning to loosen stiff muscles and joints, and reduce pain. The therapeutic effects of BioFlexor will allow you to become more active and return to normal activities of daily living.

WARNINGS

For External use only. Do not swallow. If Accidentally ingested, induce vomiting. Call a physician or poison control center immediately. If irritation develops, discontinue use of this product and consult a physician. Do not use on open sores, wounds, irritated or broken skin. Do not use with other creams, gels, ointments, topical medications, heating pads or other heat producing devices. Avoid contact with eyes or mucous membrane. Store in a cool dry place. Keep out of reach of children to avoid accidental poisoning. BioFlexor gel is contraindicated in patients with a known hypersensitivity to menthol. For children under 2, pregnant or nursing mothers, consult a physician.

HOW SUPPLIED

0.25 oz (7.5 Gm) Jars NDC# 62391-001-10
2.25 oz (67.5 Gm) Jars NDC# 62391-001-02
4.5 oz (135 Gm) Jars NDC# 62391-001-04
32 oz (960 Gm) Jars NDC# 62391-001-30

TO PLACE ORDERS:
To place orders, please call customer service at:
1-800-909-9854
Or Fax orders to:
1-800-316-7853

Visit our website at:
www.bioflexor.com

Mfg. by HEALTH CARE LABS, INC.
P.O. Box 1734, Cleveland, TX 77328

Keep out of reach of children.

PATIENT INFORMATION

BioFlexor®
Deep Penetrating
Effective Pain Relief Gel
Description: BioFlexor® gel is an OTC topical analgesic preparation which delivers deep penetrating, effective pain relief. BioFlexor® is a unique product from several viewpoints. In developing BioFlexor®, our main focus was to formulate a potent topical analgesic agent that would minimize the need for oral narcotic analgesics. The result is an exceptional product that truly helps those individuals suffering from the pain associated with the spectrum of medical conditions from arthritis to muscle aches and pain, simple back aches, strains, bruises, and sprains. Menthol is the only listed active ingredient on the BioFlexor® label. The other all natural components work synergistically to produce the pain relieving activity. Another unique aspect of BioFlexor® relates to the immediate and long-lasting pain relief without the side effects of lingering scent (Methyl Salicylate rubs, ie. Ben Gay), burning sensation (Capsaicin ie. Zostrix, Theragesic, Icy-Hot), greasy residue (ie. Aspercreme, Ben-Gay), and dry skin (alcohol formulations, ie. Biofreeze). The BioFlexor® formulation contains no alcohol, capsaicin, or methyl salicylate.
Mechanism of Action: The initial pain relief mechanism produced by the absorption of BioFlexor® generates a topical cooling effect. This is a result of vasoconstriction of peripheral vessels in the affected areas, yielding a decreased blood flow. This action causes a decrease in temperature of the skin and subcutaneous tissues. As penetration continues, an interruption of sympathetic nerve conduction occurs, producing a warm vasodilation. This in turn increases the blood flow to muscle tissues and to the surface of the skin, promoting the healing process and rendering analgesic properties. BioFlexor® gel is contraindicated in patients with a known hypersensitivity to menthol.

How Supplied:
2.25oz (67.5gm) Jars…..NDC# 62391-001-02
4.5oz (135gm) Jars …..…NDC# 62391-001-04

TO PLACE ORDERS:
Please call Customer Service at: 1-800-909-9854
or Fax Orders to: 1-800-316-7853
or Visit our Website at: www.bioflexor.com

Mfg. By: HEALTH CARE LABORATORIES, INC.
112 S. COLLEGE AVE. #100A
CLEVELAND, TX 77327
Store at controlled room temperature 15˚-30˚C (59˚-86˚F)
*Registered trademarks are the property of their respective owners.
DRUG FACTS
Active Ingredient Purpose
Menthol 3%, Topical Analgesic
Uses
Temporarily relieves the minor aches and pains of muscles and joints associated with:
•simple backache •arthritis •strains •bruises •sprains
Warnings
For external use only.
Do Not Use:
• on wounds or damaged skin
• with a heating pad
• on a child under 12 years of age with arthritis-like conditions
Ask a doctor before use if you have redness over the affected area.
When using this product:
• avoid contact with the eyes or mucous membranes
• do not bandage tightly
Stop use and ask a doctor if:
• condition worsens or symptoms persist for more than 7 days
• symptoms clear up and occur again within a few days
• excessive skin irritation occurs
Keep out of reach of children.
If swallowed, get medical help or contact the Poison Control Center right away.
Directions
Adults and children 12 years of age and older:
• apply to affected area not more than 3 to 4 times daily.
Children under 12 years of age:
• consult a doctor
Other Information
• Store at 20°-25°C (68°-77°)
• Lot No. and Expiration Date: See Container
Inactive Ingredients
Carbopolymer, Edetate Disodium Peacock Blue MX26,
Phenoxyethanol/Paraben Blend, Polysorbate 20, Potassium Sorbate,
Proprietary Blend, Purified Water, Sodium Hydroxide

Active Ingredient: Menthol 3%

INACTIVE INGREDIENT

Inactive Ingredients: Carbopol Polymer, Edetate Disodium, Peacock Blue MX26, Phenoxyethanol/Paraben Blend, Polysorbate 20, Potassium Sorbate, Proprietary Blend, Purified Water, Sodium Hydroxide

PURPOSE

Description: BioFlexor® gel is an OTC topical analgesic preparation which delivers deep penetrating, effective pain relief. BioFlexor® is a unique product from several viewpoints. In developing BioFlexor®, our main focus was to formulate a potent topical analgesic agent that would minimize the need for oral narcotic analgesics. The result is an exceptional product that truly helps those individuals suffering from the pain associated with the spectrum of medical conditions from arthritis to muscle aches and pain, simple back aches, strains, bruises, and sprains. Menthol is the only listed active ingredient on the BioFlexor® label. The other all natural components work synergistically to produce the pain relieving activity. Another unique aspect of BioFlexor® relates to the immediate and long-lasting pain relief without the side effects of lingering scent (Methyl Salicylate rubs, ie. Ben Gay), burning sensation (Capsaicin ie. Zostrix, Theragesic, Icy-Hot), greasy residue (ie. Aspercreme, Ben-Gay), and dry skin (alcohol formulations, ie. Biofreeze).

The BioFlexor formulation contains no alcohol, capsaicin or methyl salicylate.

INDICATIONS AND USAGE

INDICATIONS: For the temporary relief of minor aches and pains of muscles and joints associated with simple backache, arthritis, strains, bruises, and sprains.

USAGE: Adults and children 12 years of age and older: Apply to affected area not more than 3 to 4 times daily. Children under 12 years of age, pregnant or nursing mothers: Consult a physician.